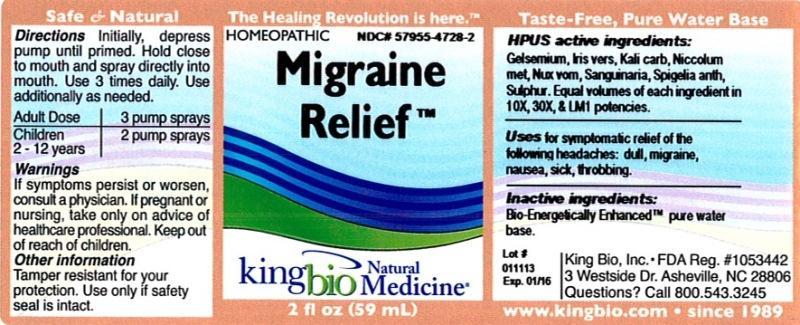 DRUG LABEL: Migraine Relief
NDC: 57955-4728 | Form: LIQUID
Manufacturer: King Bio Inc.
Category: homeopathic | Type: HUMAN OTC DRUG LABEL
Date: 20130111

ACTIVE INGREDIENTS: GELSEMIUM SEMPERVIRENS ROOT 10 [hp_X]/59 mL; IRIS VERSICOLOR ROOT 10 [hp_X]/59 mL; POTASSIUM CARBONATE 10 [hp_X]/59 mL; NICKEL 10 [hp_X]/59 mL; STRYCHNOS NUX-VOMICA SEED 10 [hp_X]/59 mL; SANGUINARIA CANADENSIS ROOT 10 [hp_X]/59 mL; SPIGELIA ANTHELMIA 10 [hp_X]/59 mL; SULFUR 10 [hp_X]/59 mL
INACTIVE INGREDIENTS: WATER

Migraine Relief

HPUS Active Ingredients

Gelsemium sempervirens, Iris versicolor, Kali carbonicum, Niccolum metallicum, Nux vomica, Sanguinaria canadensis, Spigelia anthelmia and Sulphur. Equal volumes of each ingredient in 10X, 30X and LM1 potencies.

Inactive Ingredient

Bio-Energetically Enhanced™ pure water base.

PURPOSE

Uses for symptomatic relief of the following headaches:

- dull
- migraine
- nausea
- sick
- throbbing

Warnings

If symptoms persist or worsen, consult a physician. If pregnant or nursing, take only on advice of healthcare professional. Keep out of reach of children.

Other Information

Tamper resistant for your protection. Use only if safety seal is intact.

Keep out of reach of children.

Directions

Initially, depress pump until primed. Hold close to mouth and spray directly into mouth. Use 3 times daily. Use additionally as needed.

Adult Dose 3 pump sprays

Children 2 - 12 years 2 pump sprays

INDICATIONS AND USAGE

Uses for symptomatic relief of the following headaches: dull, migraine, nausea, sick and throbbing.

PACKAGE LABEL

King Bio Inc.

3 Westside Drive

Asheville, NC 28806

Questions? Call 800.543.3245

www.kingbio.com